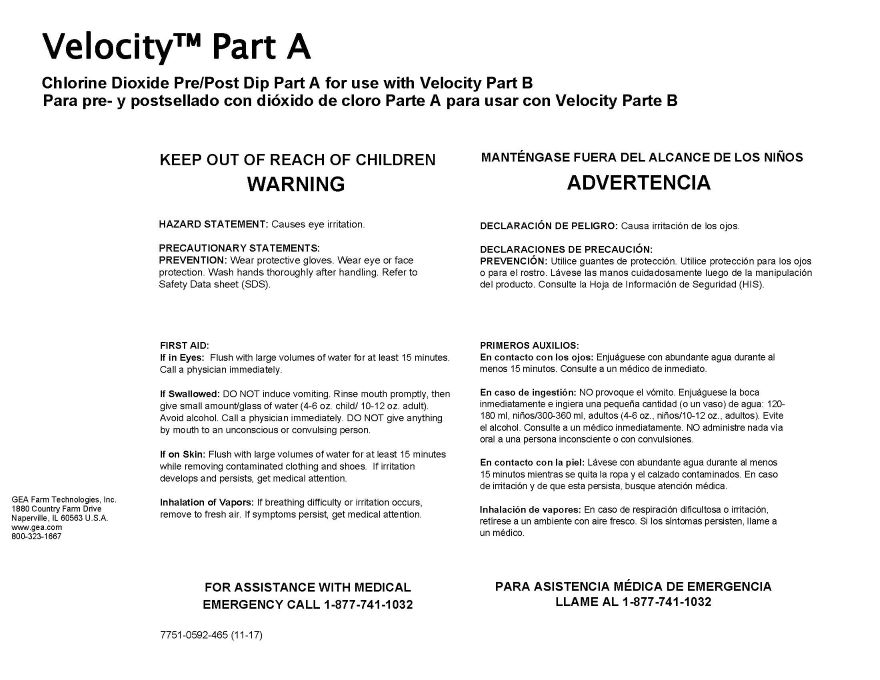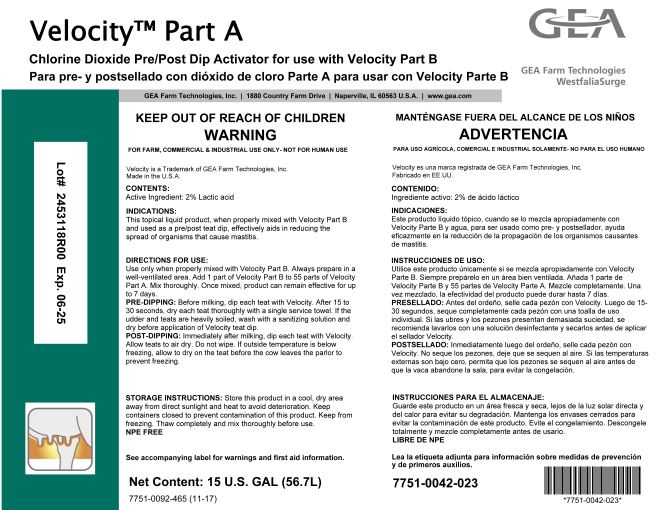 DRUG LABEL: GEA Velocity Part A
NDC: 51070-7010 | Form: LIQUID
Manufacturer: GEA Farm Technologies, Inc.
Category: animal | Type: OTC ANIMAL DRUG LABEL
Date: 20240604

ACTIVE INGREDIENTS: LACTIC ACID 2.2 g/100 g
INACTIVE INGREDIENTS: UREA; FD&C YELLOW NO. 5; XANTHAN GUM; DODECYLBENZENESULFONIC ACID; PIGMENT GREEN 7; FD&C BLUE NO. 1

Velocity Part A

ACTIVE INGREDIENT

CONTENTS:

ACTIVE INGREDIENT: 2% Lactic acid

Net Content: 15 U.S. GAL (56.7L)

KEEP OUT OF REACH OF CHILDREN

WARNING

PRECAUTIONS

HAZARD STATEMENT: Causes eye irritation.

PRECAUTIONARY STATEMENTS:

PREVENTION: Wear protective gloves. Wear eye or face protection. Wash hands thoroughly after handling. Refer to Safety Data sheet (SDS).

USER SAFETY WARNINGS

FIRST AID:

If in Eyes: Flush with large volumes of water for at least 15 minutes. Call a physician immediately.
If Swallowed: DO NOT induce vomiting. Rinse mouth promptly, then give small amount/glass of water (4-6 oz. child / 10-12 oz. adult). Avoid alcohol. Call a physician immediately. DO NOT give anything by mouth to an unconscious or convulsing person.
If on Skin: Flush with large volumes of water for at least 15 minutes while removing contaminated clothing and shoes. If irritation develops and persists, get medical attention.
Inhalation of Vapors: If breathing difficulty or irritation occurs, remove to fresh air. If symptoms persist, get medical attention.

FOR ASSISTANCE WITH MEDICAL EMERGENCY

CALL 1-877-741-1032

FOR FARM, COMMERCIAL & INDUSTRIAL USE ONLY- NOT FOR HUMAN USE

Velocity is a Trademark of GEA Farm Technologies, Inc.

Made in U.S.A.

INDICATIONS AND USAGE

INDICATIONS: This topical liquid product, when properly mixed with Velocity Part B and used as a pre/post teat dip, effectively aids in reducing the spread of organisms that cause mastitis.

DOSAGE AND ADMINISTRATION

DIRECTIONS FOR USE: Use only when properly mixed with Velocity Part B. Always prepare mixture in a well-ventilated area. Add 1 part of Velocity Part B to 55 parts of Velocity Part A. Mix thoroughly. Once mixed, product can remain effective for up to 7 days.

PRE-DIPPING: Before milking, dip each teat with Velocity. After 15 to 30 seconds, dry each treat thoroughly with a single service towel. If the udder and teats are heavily soiled, wash with a sanitizing solution and dry before application of Velocity teat dip.

POST-DIPPING: Immediately after milking, dip each teat with Velocity. Allow teats to air dry. Do not wipe. If outside temperature is below freezing, allow to air dry on the teat before the cow leaves the parlor to prevent freezing.

STORAGE INSTRUCTIONS:

Store this product in a cool, dry area away from direct sunlight and heat to avoid deterioration. Keep containers closed to prevent contamination of this product. Keep from freezing. Thaw completely and mix thoroughly before use.

NPE FREE

See accompanying label for warnings and first aid information.

7751-0092-465 (11-17)

GEA Farm Technologies, Inc. • 1880 Country Farm Drive • Naperville, IL 60563 U.S.A • www.gea.com

7751-0042-023

GEA Farm Technologies, Inc.

1880 Country Farm Dr.

Naperville, IL 60563 U.S.A.

www.gea.com

800-323-1667

7751-0592-465 (11-17)

PACKAGE LABEL

Velocity™ Part A

Chlorine Dioxide Pre/Post Dip Part A for use with Velocity Part B